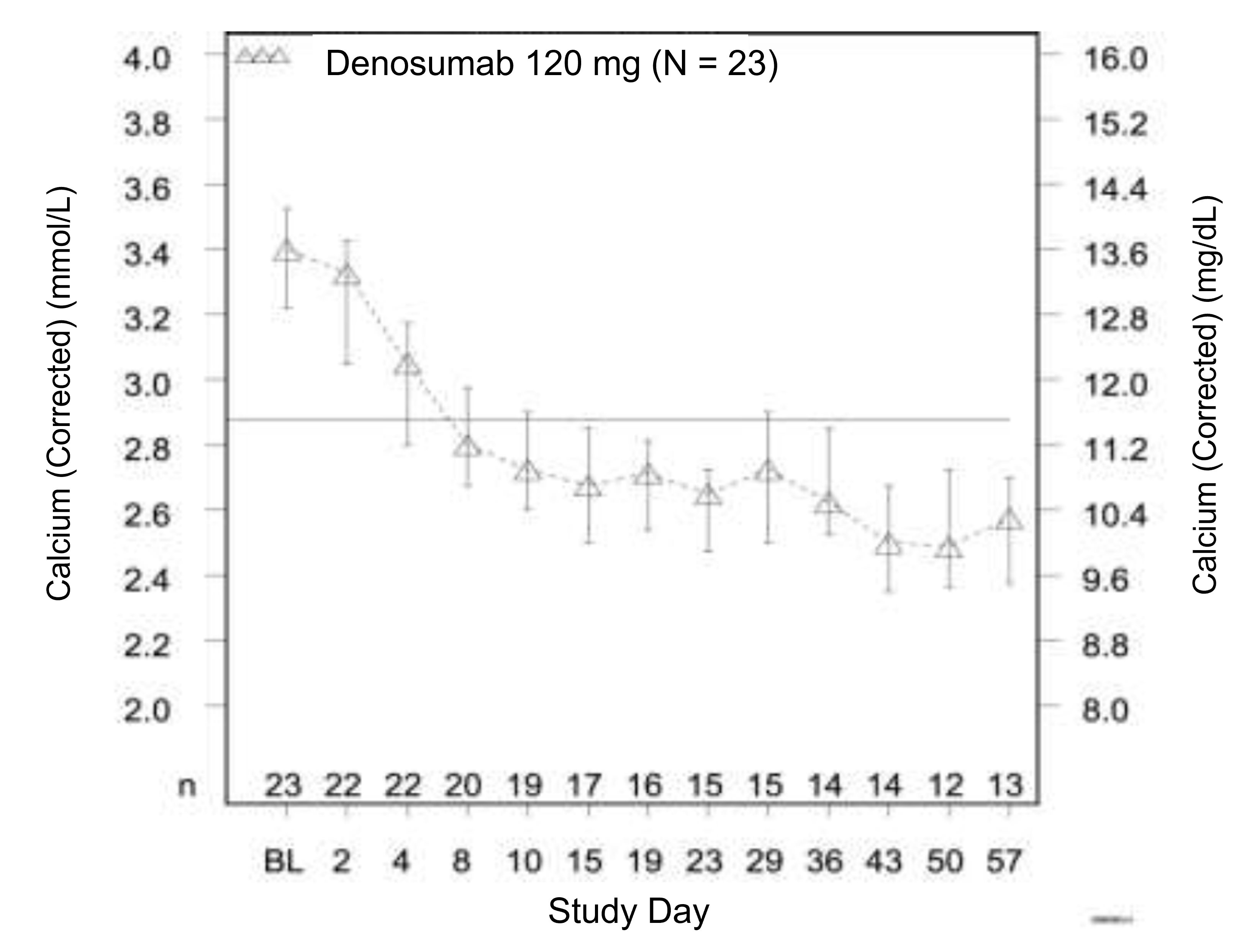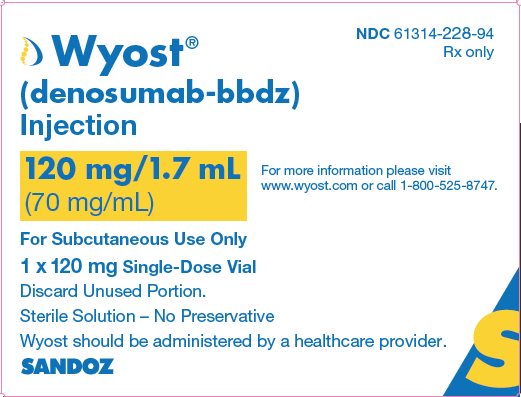 DRUG LABEL: WYOST
NDC: 61314-228 | Form: INJECTION
Manufacturer: Sandoz Inc
Category: prescription | Type: HUMAN PRESCRIPTION DRUG LABEL
Date: 20251030

ACTIVE INGREDIENTS: DENOSUMAB 120 mg/1.7 mL
INACTIVE INGREDIENTS: ACETIC ACID 1.85 mg/1.7 mL; POLYSORBATE 20 0.17 mg/1.7 mL; SORBITOL 78.9 mg/1.7 mL; WATER; SODIUM HYDROXIDE 0.91 mg/1.7 mL; HYDROCHLORIC ACID

HIGHLIGHTS OF PRESCRIBING INFORMATION

These highlights do not include all the information needed to use WYOST® safely and effectively. See full prescribing information for WYOST.
WYOST® (denosumab-bbdz) injection, for subcutaneous use
Initial U.S. Approval: 2024
WYOST (denosumab-bbdz) is biosimilar* to XGEVA® (denosumab).

RECENT MAJOR CHANGES

Dosage and Administration (2.1) 10/2025

Warnings and Precautions (5.1) 10/2025

1 INDICATIONS AND USAGE

Wyost is a RANK ligand (RANKL) inhibitor indicated for:

- Prevention of skeletal-related events in patients with multiple myeloma and in patients with bone metastases from solid tumors. (1.1)
- Treatment of adults and skeletally mature adolescents with giant cell tumor of bone that is unresectable or where surgical resection is likely to result in severe morbidity. (1.2, 14.3)
- Treatment of hypercalcemia of malignancy refractory to bisphosphonate therapy. (1.3)

2 DOSAGE AND ADMINISTRATION

- Wyost should be administered by a healthcare provider. (2.1)
- Wyost is intended for subcutaneous route only and should not be administered intravenously, intramuscularly, or intradermally. (2.1)
- Multiple Myeloma and Bone Metastasis from Solid Tumors: Administer 120 mg every 4 weeks as a subcutaneous injection in the upper arm, upper thigh, or abdomen. (2.2)
- Giant Cell Tumor of Bone: Administer 120 mg every 4 weeks with additional 120 mg doses on Days 8 and 15 of the first month of therapy. Administer subcutaneously in the upper arm, upper thigh, or abdomen. (2.3)
- Administer calcium and vitamin D as necessary to treat or prevent hypocalcemia. (2.2, 2.3)
- Hypercalcemia of Malignancy: Administer 120 mg every 4 weeks with additional 120 mg doses on Days 8 and 15 of the first month of therapy. Administer subcutaneously in the upper arm, upper thigh, or abdomen. (2.4)

3 DOSAGE FORMS AND STRENGTHS

- Injection: 120 mg/1.7 mL (70 mg/mL) solution in a single-dose vial. (3)

4 CONTRAINDICATIONS

- Hypocalcemia. (4.1)
- Known clinically significant hypersensitivity to denosumab products. (4.2)

5 WARNINGS AND PRECAUTIONS

- Drug Products with Same Active Ingredient: Patients receiving Wyost should not receive other denosumab products concomitantly. (5.1)
- Hypersensitivity reactions including anaphylaxis may occur. Discontinue permanently if a clinically significant reaction occurs. (5.2)
- Hypocalcemia: Denosumab products can cause severe symptomatic hypocalcemia. Fatal cases have been reported with denosumab products use. Correct hypocalcemia prior to initiating Wyost. Monitor calcium levels during therapy, especially in the first weeks of initiating therapy, and adequately supplement all patients with calcium and vitamin D. (5.3)
- Osteonecrosis of the jaw (ONJ) has been reported in patients receiving denosumab products. Perform an oral examination prior to starting Wyost. Monitor for symptoms. Avoid invasive dental procedures during treatment with Wyost. (5.4)
- Atypical femoral fracture: Evaluate patients with thigh or groin pain to rule out a femoral fracture. (5.5)
- Hypercalcemia Following Treatment Discontinuation in Patients with Giant Cell Tumor of Bone and in Patients with Growing Skeletons: Monitor patients for signs and symptoms of hypercalcemia, and manage as clinically appropriate. (5.6, 8.4)
- Multiple Vertebral Fractures (MVF) Following Treatment Discontinuation: When Wyost treatment is discontinued, evaluate the individual patient’s risk for vertebral fractures. (5.7)
- Embryo-Fetal Toxicity: Can cause fetal harm. Advise females of reproductive potential of potential risk to the fetus and to use effective contraception. (5.8, 8.1, 8.3)

6 ADVERSE REACTIONS

- Bone Metastasis from Solid Tumors: Most common adverse reactions (≥ 25%) were fatigue/asthenia, hypophosphatemia, and nausea. (6.1)
- Multiple Myeloma: Most common adverse reactions (≥ 10%) were diarrhea, nausea, anemia, back pain, thrombocytopenia, peripheral edema, hypocalcemia, upper respiratory tract infection, rash, and headache. (6.1)
- Giant Cell Tumor of Bone: Most common adverse reactions (≥ 10%) were arthralgia, headache, nausea, back pain, fatigue, and pain in extremity. (6.1)
- Hypercalcemia of Malignancy: Most common adverse reactions (> 20%) were nausea, dyspnea, decreased appetite, headache, peripheral edema, vomiting, anemia, constipation, and diarrhea. (6.1)

To report SUSPECTED ADVERSE REACTIONS, contact Sandoz Inc. at 1-800-525-8747 or FDA at 1-800-FDA-1088 or www.fda.gov/medwatch.

8 USE IN SPECIFIC POPULATIONS

- Pediatric patients: Recommended only for treatment of skeletally mature adolescents with giant cell tumor of bone. (8.4)
- Renal impairment: Patients with creatinine clearance less than 30 mL/min or receiving dialysis are at risk for hypocalcemia. Adequately supplement with calcium and vitamin D. (8.6)

* Biosimilar means that the biological product is approved based on data demonstrating that it is highly similar to an FDA-approved biological product, known as a reference product, and that there are no clinically meaningful differences between the biosimilar product and the reference product. Biosimilarity of WYOST has been demonstrated for the condition(s) of use (e.g., indication(s), dosing regimen(s)), strength(s), dosage form(s), and route(s) of administration described in its Full Prescribing Information.

FULL PRESCRIBING INFORMATION

1 INDICATIONS AND USAGE

1.1 Multiple Myeloma and Bone Metastasis from Solid Tumors

Wyost is indicated for the prevention of skeletal-related events in patients with multiple myeloma and in patients with bone metastases from solid tumors.

1.2 Giant Cell Tumor of Bone

Wyost is indicated for the treatment of adults and skeletally mature adolescents with giant cell tumor of bone that is unresectable or where surgical resection is likely to result in severe morbidity [see Clinical Trials (14.2)].

1.3 Hypercalcemia of Malignancy

Wyost is indicated for the treatment of hypercalcemia of malignancy refractory to bisphosphonate therapy.

2 DOSAGE AND ADMINISTRATION

2.1 Important Administration Instructions

Wyost should be administered by a healthcare provider.

Wyost is intended for subcutaneous route only and should not be administered intravenously, intramuscularly, or intradermally.

2.2 Multiple Myeloma and Bone Metastasis from Solid Tumors

The recommended dose of Wyost is 120 mg administered as a subcutaneous injection every 4 weeks in the upper arm, upper thigh, or abdomen.

Administer calcium and vitamin D as necessary to treat or prevent hypocalcemia [see Warnings and Precautions (5.3)].

2.3 Giant Cell Tumor of Bone

The recommended dose of Wyost is 120 mg administered every 4 weeks with additional 120 mg doses on Days 8 and 15 of the first month of therapy. Administer subcutaneously in the upper arm, upper thigh, or abdomen.

Administer calcium and vitamin D as necessary to treat or prevent hypocalcemia [see Warnings and Precautions (5.3)].

2.4 Hypercalcemia of Malignancy

The recommended dose of Wyost is 120 mg administered every 4 weeks with additional 120 mg doses on Days 8 and 15 of the first month of therapy. Administer subcutaneously in the upper arm, upper thigh, or abdomen.

2.5 Preparation and Administration

Parenteral drug products should be inspected visually for particulate matter and discoloration prior to administration, whenever solution and container permit. Wyost is a clear to slightly opalescent and colorless to slightly yellowish to slightly brownish solution. Do not use if the solution is discolored or cloudy or if the solution contains visible particles or foreign particulate matter.

Prior to administration, Wyost may be removed from the refrigerator and brought to room temperature up to 25°C (77°F) by standing in the original container. This generally takes 15 to 30 minutes. Do not warm Wyost in any other way [see How Supplied/Storage and Handling (16)].

Use a 27-gauge needle to withdraw and inject the entire contents of the vial. Do not re-enter the vial. Discard vial after single entry.

3 DOSAGE FORMS AND STRENGTHS

Injection: 120 mg/1.7 mL (70 mg/mL) clear to slightly opalescent and colorless to slightly yellowish to slightly brownish solution in a single-dose vial.

4 CONTRAINDICATIONS

4.1 Hypocalcemia

Pre-existing hypocalcemia must be corrected prior to initiating therapy with Wyost [see Warnings and Precautions (5.3)].

4.2 Hypersensitivity

Wyost is contraindicated in patients with known clinically significant hypersensitivity to denosumab products [see Warnings and Precautions (5.2) and Adverse Reactions (6.2)].

5 WARNINGS AND PRECAUTIONS

5.1 Drug Products with Same Active Ingredient

Patients receiving Wyost should not receive other denosumab products concomitantly.

5.2 Hypersensitivity

Clinically significant hypersensitivity including anaphylaxis has been reported with use of denosumab products. Reactions may include hypotension, dyspnea, upper airway edema, lip swelling, rash, pruritus, and urticaria. If an anaphylactic or other clinically significant allergic reaction occurs, initiate appropriate therapy and discontinue Wyost therapy permanently [see Contraindications (4.2) and Adverse Reactions (6.2)].

5.3 Hypocalcemia

Denosumab products can cause severe symptomatic hypocalcemia, and fatal cases have been reported. Correct pre-existing hypocalcemia prior to Wyost treatment. Monitor calcium levels, throughout Wyost therapy, especially in the first weeks of initiating therapy, and administer calcium, magnesium, and vitamin D as necessary. Concomitant use of calcimimetics and other drugs that can lower calcium levels may worsen hypocalcemia risk and serum calcium should be closely monitored. Advise patients to contact a healthcare provider for symptoms of hypocalcemia [see Contraindications (4.1), Adverse Reactions (6.1, 6.2), and Patient Counseling Information (17)].

An increased risk of hypocalcemia has been observed in clinical trials of patients with increasing renal dysfunction, most commonly with severe dysfunction (creatinine clearance less than 30 mL/min and/or on dialysis), and with inadequate/no calcium supplementation. Monitor calcium levels and calcium and vitamin D intake [see Adverse Reactions (6.1), Use in Specific Populations (8.6), and Clinical Pharmacology (12.3)].

5.4 Osteonecrosis of the Jaw (ONJ)

Osteonecrosis of the jaw (ONJ) has been reported in patients receiving denosumab products, manifesting as jaw pain, osteomyelitis, osteitis, bone erosion, tooth or periodontal infection, toothache, gingival ulceration, or gingival erosion. Persistent pain or slow healing of the mouth or jaw after dental surgery may also be manifestations of ONJ. In clinical trials in patients with cancer, the incidence of ONJ was higher with longer duration of exposure [see Adverse Reactions (6.1)]. Seventy-nine percent of patients with ONJ had a history of tooth extraction, poor oral hygiene, or use of a dental appliance as a predisposing factor. Other risk factors for the development of ONJ include immunosuppressive therapy, treatment with angiogenesis inhibitors, systemic corticosteroids, diabetes, and gingival infections. Similarly, for denosumab-treated patients with multiple myeloma that developed ONJ, 58% had a history of invasive dental procedures as a predisposing factor.

Perform an oral examination and appropriate preventive dentistry prior to the initiation of Wyost and periodically during Wyost therapy. Advise patients regarding oral hygiene practices. Avoid invasive dental procedures during treatment with Wyost. Consider temporary discontinuation of Wyost therapy if an invasive dental procedure must be performed. There are no data available to suggest the optimal duration of treatment interruption.

Patients who are suspected of having or who develop ONJ while on Wyost should receive care by a dentist or an oral surgeon. In these patients, extensive dental surgery to treat ONJ may exacerbate the condition. Clinical judgment of the treating healthcare provider should guide the management plan of each patient based on individual risk/benefit assessment.

5.5 Atypical Subtrochanteric and Diaphyseal Femoral Fracture

Atypical femoral fracture has been reported with denosumab products [see Adverse Reactions (6.1)]. These fractures can occur anywhere in the femoral shaft from just below the lesser trochanter to above the supracondylar flare and are transverse or short oblique in orientation without evidence of comminution.

Atypical femoral fractures most commonly occur with minimal or no trauma to the affected area. They may be bilateral and many patients report prodromal pain in the affected area, usually presenting as dull, aching thigh pain, weeks to months before a complete fracture occurs. A number of reports note that patients were also receiving treatment with glucocorticoids (e.g. prednisone) at the time of fracture.

During Wyost treatment, patients should be advised to report new or unusual thigh, hip, or groin pain. Any patient who presents with thigh or groin pain should be suspected of having an atypical fracture and should be evaluated to rule out an incomplete femur fracture. Patient presenting with an atypical femur fracture should also be assessed for symptoms and signs of fracture in the contralateral limb. Interruption of Wyost therapy should be considered, pending a risk/benefit assessment, on an individual basis.

5.6 Hypercalcemia Following Treatment Discontinuation in Patients with Giant Cell Tumor of Bone and in Patients with Growing Skeletons

Clinically significant hypercalcemia requiring hospitalization and complicated by acute renal injury has been reported in denosumab product-treated patients with giant cell tumor of bone and patients with growing skeletons. Hypercalcemia has been reported within the first year after treatment discontinuation. After treatment is discontinued, monitor patients for signs and symptoms of hypercalcemia, assess serum calcium periodically, reevaluate the patient’s calcium and vitamin D supplementation requirements and manage patients as clinically appropriate [see Adverse Reactions (6) and Use in Specific Populations (8.4)].

5.7 Multiple Vertebral Fractures (MVF) Following Treatment Discontinuation

Multiple vertebral fractures (MVF) have been reported following discontinuation of treatment with denosumab products. Patients at higher risk for MVF include those with risk factors for or a history of osteoporosis or prior fractures.

When Wyost treatment is discontinued, evaluate the individual patient’s risk for vertebral fractures [see Patient Counseling Information (17)].

5.8 Embryo-Fetal Toxicity

Based on data from animal studies and its mechanism of action, denosumab products can cause fetal harm when administered to a pregnant woman. In animal reproduction studies, administration of denosumab to cynomolgus monkeys throughout pregnancy at a dose 25-fold higher than the recommended human dose of denosumab based on body weight resulted in increased fetal loss, stillbirths, and postnatal mortality, along with evidence of absent peripheral lymph nodes, abnormal bone growth and decreased neonatal growth.

Verify the pregnancy status of females of reproductive potential prior to the initiation of Wyost. Advise pregnant women and females of reproductive potential that exposure to Wyost during pregnancy or within 5 months prior to conception can result in fetal harm. Advise females of reproductive potential to use effective contraception during therapy, and for at least 5 months after the last dose of Wyost [see Use in Specific Populations (8.1, 8.3) and Clinical Pharmacology (12.1)].

6 ADVERSE REACTIONS

The following adverse reactions are discussed below and elsewhere in the labeling:

- Hypersensitivity [see Warnings and Precautions (5.2)]
- Hypocalcemia [see Warnings and Precautions (5.3) and Use in Specific Populations (8.6)]
- Osteonecrosis of the Jaw [see Warnings and Precautions (5.4)]
- Atypical Subtrochanteric and Diaphyseal Femoral Fracture [see Warnings and Precautions (5.5)]
- Hypercalcemia following treatment discontinuation in patients with giant cell tumor of bone and in patients with growing skeletons [see Warnings and Precautions (5.6) and Use in Specific Populations (8.4)]
- Multiple vertebral fractures (MVF) following treatment discontinuation [see Warnings and Precautions (5.7)]

6.1 Clinical Trials Experience

Because clinical trials are conducted under widely varying conditions, adverse reaction rates observed in the clinical trials of a drug cannot be directly compared to rates in the clinical trials of another drug and may not reflect the rates observed in practice.

Bone Metastasis from Solid Tumors

The safety of denosumab was evaluated in three randomized, double-blind, double-dummy trials [see Clinical Trials (14.1)] in which a total of 2841 patients with bone metastasis from prostate cancer, breast cancer, or other solid tumors, or lytic bony lesions from multiple myeloma received at least one dose of denosumab. In Studies 20050136, 20050244, and 20050103, patients were randomized to receive either 120 mg of denosumab every 4 weeks as a subcutaneous injection or 4 mg (dose adjusted for reduced renal function) of zoledronic acid every 4 weeks by intravenous (IV) infusion. Entry criteria included serum calcium (corrected) from 8 to 11.5 mg/dL (2 to 2.9 mmol/L) and creatinine clearance 30 mL/min or greater. Patients who had received IV bisphosphonates were excluded, as were patients with prior history of ONJ or osteomyelitis of the jaw, an active dental or jaw condition requiring oral surgery, non-healed dental/oral surgery, or any planned invasive dental procedure. During the study, serum chemistries including calcium and phosphorus were monitored every 4 weeks. Calcium and vitamin D supplementation was recommended but not required.

The median duration of exposure to denosumab was 12 months (range: 0.1-41) and median duration on-study was 13 months (range: 0.1-41). Of patients who received denosumab, 46% were female. Eighty-five percent were White, 5% Hispanic/Latino, 6% Asian, and 3% Black. The median age was 63 years (range: 18-93). Seventy-five percent of patients who received denosumab received concomitant chemotherapy.

The most common adverse reactions in patients (incidence greater than or equal to 25%) were fatigue/asthenia, hypophosphatemia, and nausea (see Table 1). The most common serious adverse reaction was dyspnea. The most common adverse reactions resulting in discontinuation of denosumab were osteonecrosis and hypocalcemia.

Table 1. Selecteda Adverse Reactions of Any Severity (Studies 20050136, 20050244, and 20050103)
Body System | Denosumab n = 2841 % | Zoledronic Acid n = 2836 %
GASTROINTESTINAL
Nausea | 31 | 32
Diarrhea | 20 | 19
GENERAL
Fatigue/Asthenia | 45 | 46
INVESTIGATIONS
Hypocalcemiab | 18 | 9
Hypophosphatemiab | 32 | 20
NEUROLOGICAL
Headache | 13 | 14
RESPIRATORY
Dyspnea | 21 | 18
Cough | 15 | 15
a Adverse reactions reported in at least 10% of patients receiving denosumab in Studies 20050136, 20050244, and 20050103, and meeting one of the following criteria:
- At least 1% greater incidence in denosumab-treated patients, or
- Between-group difference (either direction) of less than 1% and more than 5% greater incidence in patients treated with zoledronic acid compared to placebo (US Prescribing Information for zoledronic acid)
b Laboratory-derived and below the central laboratory lower limit of normal [8.3-8.5 mg/dL (2.075 - 2.125 mmol/L) for calcium and 2.2-2.8 mg/dL (0.71-0.9 mmol/L) for phosphorus]

Severe Mineral/Electrolyte Abnormalities

- Severe hypocalcemia (corrected serum calcium less than 7 mg/dL or less than 1.75 mmol/L) occurred in 3.1% of patients treated with denosumab and 1.3% of patients treated with zoledronic acid. Of patients who experienced severe hypocalcemia, 33% experienced 2 or more episodes of severe hypocalcemia and 16% experienced 3 or more episodes [see Warnings and Precautions (5.3) and Use in Specific Populations (8.6)].
- Severe hypophosphatemia (serum phosphorus less than 2 mg/dL or less than 0.6 mmol/L) occurred in 15% of patients treated with denosumab and 7% of patients treated with zoledronic acid.

Osteonecrosis of the Jaw (ONJ)

In the primary treatment phases of Studies 20050136, 20050244, and 20050103, ONJ was confirmed in 1.8% of patients in the denosumab group (median exposure of 12.0 months; range: 0.1-41) and 1.3% of patients in the zoledronic acid group. The trials in patients with breast (Study 20050136) or prostate (Study 20050103) cancer included an open-label extension treatment phase where patients were offered denosumab 120 mg once every 4 weeks (median overall exposure of 14.9 months; range: 0.1-67.2). The patient-year adjusted incidence (number of events per 100 patient years) of confirmed ONJ was 1.1% during the first year of treatment, 3.7% in the second year, and 4.6% per year thereafter. The median time to ONJ was 20.6 months (range: 4-53) [see Warnings and Precautions (5.4)].

In a placebo-controlled clinical trial with an extension treatment phase evaluating denosumab for the prevention of bone metastases in patients with non-metastatic prostate cancer (a patient population for which denosumab is not indicated), with longer treatment exposure of up to 7 years, the patient-year adjusted incidence (number of events per 100 patient years) of confirmed ONJ was 1.1% during the first year of treatment, 3% in the second year, and 7% per year thereafter.

Atypical Subtrochanteric and Diaphyseal Fracture

In the clinical trial program, atypical femoral fracture has been reported in patients treated with denosumab and the risk increased with longer duration of treatment. Events have occurred during treatment and after treatment was discontinued [see Warnings and Precautions (5.5)].

Multiple Myeloma

The safety of denosumab was evaluated in an international, randomized (1:1), double-blind, active-controlled trial of patients with newly diagnosed multiple myeloma with treatment through disease progression [see Clinical Trials (14.2)]. In this trial, patients received 120 mg denosumab every 4 weeks as a subcutaneous injection (n = 850) or 4 mg (dose adjusted for renal function) of zoledronic acid intravenously (IV) every 4 weeks by IV infusion (n = 852). Entry criteria included serum calcium (corrected) from 8 to 11.5 mg/dL (2 to 2.9 mmol/L) and creatinine clearance 30 mL/min or greater. Patients who had received IV bisphosphonates were excluded, as were patients with prior history of ONJ or osteomyelitis of the jaw, an active dental or jaw condition requiring oral surgery, non-healed dental/oral surgery, or any planned invasive dental procedure. During the study, serum chemistries including calcium and phosphorus were monitored every 4 weeks. Calcium and vitamin D supplementation was recommended but not required.

The median duration of exposure to denosumab was 16 months (range: 1-50) and median duration on-study was 17 months (range: 0-49). Of patients who received denosumab, 46% were female, 83% were White, 13% Asian, 3% Black or African American, and 4% Hispanic/Latino. The median age of the patients randomized to denosumab was 63 years (range: 29-91) and all patients who received denosumab received concomitant anti-myeloma chemotherapy.

The adverse reaction profile of denosumab in patients with multiple myeloma, Study 20090482, was similar to that observed in Studies 20050136, 20050244, and 20050103. The most common adverse reactions (incidence ≥ 10%) were diarrhea (34%), nausea (32%), anemia (22%), back pain (21%), thrombocytopenia (19%), peripheral edema (17%), hypocalcemia (16%), upper respiratory tract infection (15%), rash (14%), and headache (11%). The most common serious adverse reaction (incidence ≥ 5%) was pneumonia (8%). The most common adverse reaction resulting in discontinuation of denosumab (≥ 1%) was osteonecrosis of the jaw.

Hypocalcemia and Hypophosphatemia

Severe hypocalcemia (corrected serum calcium less than 7 mg/dL or less than 1.75 mmol/L) and severe hypophosphatemia (serum phosphorus less than 2 mg/dL or less than 0.6 mmol/L) occurred in 2% and 21% patients treated with denosumab, respectively.

Osteonecrosis of the Jaw (ONJ)

In the primary treatment phase of Study 20090482, ONJ was confirmed in 4.1% of patients in the denosumab group (median exposure of 16 months; range: 1-50) and 2.8% of patients in the zoledronic acid group (median 15 months, range: 1-45 months). At the completion of the double-blind treatment phase of Study 20090482, the patient-year adjusted incidence (number of events per 100 patient years) of confirmed ONJ in the denosumab group (median exposure of 19.4 months; range: 1-52) was 2% during the first year of treatment, 5% in the second year, and 4.5% per year thereafter. The median time to ONJ was 18.7 months (range: 1-44) [see Warnings and Precautions (5.4)].

Giant Cell Tumor of Bone

The safety of denosumab was evaluated in two single-arm trials (Study 20062004 and Study 20040215) [see Clinical Trials (14.3)] in which a total of 548 adult or skeletally mature adolescent patients with giant cell tumor of bone received at least 1 dose of denosumab. Patients received 120 mg denosumab subcutaneously every 4 weeks with additional 120 mg doses on Days 8 and 15 of the first month of therapy. Patients receiving concurrent bisphosphonate therapy were excluded from enrollment in both studies. Patients with prior history of ONJ or osteomyelitis of the jaw, an active dental or jaw condition requiring oral surgery, non-healed dental/oral surgery, or any planned invasive dental procedure were excluded from enrollment in Study 20040215. During the trial, serum chemistries including calcium and phosphorus were monitored every 4 weeks. Calcium and vitamin D supplementation was recommended but not required.

Of the 548 patients who received denosumab, 467 patients were treated with denosumab for ≥ 1 year, 323 patients for ≥ 2 years, and 255 patients for ≥ 3 years. The median number of doses received was 33 (range: 4-138 doses) and the median number of months on-study was 60 (range: 0-140 months). Fifty-seven percent of the enrolled patients were women and 82% were White. The median age was 33 years (range: 13-83 years); a total of 19 patients were skeletally mature adolescents (12 to < 17 years of age).

The common adverse reaction profile of denosumab in patients with giant cell tumor of bone was generally similar to that reported in Studies 20050136, 20050244, and 20050103. The most common adverse reactions in patients (incidence ≥ 10%) were arthralgia, back pain, pain in extremity, fatigue, headache, nausea, nasopharyngitis, musculoskeletal pain, toothache, vomiting, hypophosphatemia, constipation, diarrhea, and cough. The most frequent serious adverse reactions were osteonecrosis of the jaw (3.6%), bone giant cell tumor (1.5%), anemia (1.1%), pneumonia (0.9%), and back pain (0.9%). The most frequent adverse reactions resulting in discontinuation of denosumab was osteonecrosis of the jaw (incidence of 3.6%). The adverse reaction profile appeared similar in skeletally mature adolescents and adults.

Hypocalcemia and Hypophosphatemia

- Moderate to severe hypocalcemia (corrected serum calcium less than 8 mg/dL or less than 2 mmol/L) occurred in 5% of patients treated with denosumab.
- Severe hypophosphatemia (serum phosphorus less than 2 to 1 mg/dL or less than 0.6 to 0.3 mmol/L) occurred in 20% of patients treated with denosumab.

Osteonecrosis of the Jaw (ONJ)

In the pooled analysis of Study 20062004 and Study 20040215, ONJ was confirmed in 7% of patients who received denosumab (median number of doses received: 33; range: 4-138 doses).

Study 20140114 (NCT03301857) was a 5-year long term follow-up study for patients (n = 85) who completed Study 20062004. In Study 20062004 and Study 20140114 combined, ONJ was confirmed in 7% of patients who received denosumab (median time on trial 62.2 months (range 0-173). The combined patient-year adjusted incidence (number of events per 100 patient years) of confirmed ONJ was 0.2% during the first year of treatment, 1.5% in the second year, 1.8% in the third year, 2.1% in the fourth year, 1.4% in the fifth year, and 1.5% thereafter [see Warnings and Precautions (5.4)].

Atypical Subtrochanteric and Diaphyseal Fracture

In the pooled analysis of Study 20062004 and Study 20040215, atypical femoral fracture was observed in 0.9% of patients who received denosumab (median number of doses received: 33; range: 4-138 doses).

In Study 20062004 and Study 20140114, the combined incidence of confirmed atypical femoral fracture was 1.3% of patients who received denosumab [see Warnings and Precautions (5.5)].

Hypercalcemia Following Treatment Discontinuation

In the pooled safety population, 0.7% of patients experienced serious adverse events of hypercalcemia > 30 days following treatment discontinuation that was recurrent in some patients [see Warnings and Precautions (5.6)].

Hypercalcemia of Malignancy

Denosumab was evaluated in an open-label, single-arm trial (Study 20070315) in which 33 patients with hypercalcemia of malignancy (with or without bone metastases) refractory to treatment with intravenous bisphosphonate therapy were enrolled [see Clinical Trials (14.4)].

The adverse reaction profile of denosumab in patients with hypercalcemia of malignancy was similar to that reported in Studies 20050136, 20050244, 20050103, 20062004, and 20040215. Adverse reactions occurring in greater than 20% of patients were nausea (30%), dyspnea (27%), decreased appetite (24%), headache (24%), peripheral edema (24%), vomiting (24%), anemia (21%), constipation (21%), and diarrhea (21%). The following adverse reactions of Grade 3 or greater severity related to study therapy were reported on-study: fatigue (3%) and infection (6%). Grade 3 laboratory abnormalities included hypomagnesemia (3%), hypokalemia (3%), and hypophosphatemia (76%) of patients. No deaths on-study were related to denosumab therapy.

6.2 Postmarketing Experience

The following adverse reactions have been identified during post-approval use of denosumab products. Because these reactions are reported voluntarily from a population of uncertain size, it is not always possible to reliably estimate their frequency or establish a causal relationship to drug exposure.

- Hypocalcemia: Severe symptomatic hypocalcemia, including fatal cases [see Contraindications (4.1) and Warnings and Precautions (5.3)].
- Hypercalcemia: Severe symptomatic hypercalcemia following treatment discontinuation can occur [see Adverse Reactions (6) and Warnings and Precautions (5.6)].
- Hypersensitivity, including anaphylactic reactions [see Contraindications (4.2) and Warnings and Precautions (5.2)].
- Musculoskeletal pain, including severe musculoskeletal pain. Positive re-challenge has been reported.
- Lichenoid drug eruptions (e.g., lichen planus-like reactions).
- Alopecia.

8 USE IN SPECIFIC POPULATIONS

8.1 Pregnancy

Risk Summary

Based on findings in animals and its mechanism of action, denosumab products can cause fetal harm when administered to a pregnant woman [see Clinical Pharmacology (12.1)]. There are insufficient data with denosumab products use in pregnant women to inform any drug associated risks for adverse developmental outcomes. In utero denosumab exposure from cynomolgus monkeys dosed monthly with denosumab throughout pregnancy at a dose 25-fold higher than the recommended human dose of denosumab based on body weight resulted in increased fetal loss, stillbirths, and postnatal mortality; and absent lymph nodes, abnormal bone growth, and decreased neonatal growth [see Data].

Apprise pregnant women of the potential risk to the fetus.

The background rate of major birth defects and miscarriage is unknown for the indicated population. In the U.S. general population, the estimated background risk of major birth defects and miscarriage in clinically recognized pregnancies is 2-4% and 15-20%, respectively.

Data

Animal Data

The effects of denosumab on prenatal development have been studied in both cynomolgus monkeys and genetically engineered mice in which RANK ligand (RANKL) expression was turned off by gene removal (a “knockout mouse”). In cynomolgus monkeys dosed subcutaneously with denosumab throughout pregnancy starting at gestational day 20 and at a pharmacologically active dose 25-fold higher than the recommended human dose of denosumab based on body weight, there was increased fetal loss during gestation, stillbirths, and postnatal mortality. Other findings in offspring included absence of axillary, inguinal, mandibular, and mesenteric lymph nodes; abnormal bone growth, reduced bone strength, reduced hematopoiesis, dental dysplasia, and tooth malalignment; and decreased neonatal growth. At birth out to one month of age, infants had measurable blood levels of denosumab (22-621% of maternal levels).

Following a recovery period from birth out to 6 months of age, the effects on bone quality and strength returned to normal; there were no adverse effects on tooth eruption, though dental dysplasia was still apparent; axillary and inguinal lymph nodes remained absent, while mandibular and mesenteric lymph nodes were present, though small; and minimal to moderate mineralization in multiple tissues was seen in one recovery animal. There was no evidence of maternal harm prior to labor; adverse maternal effects occurred infrequently during labor. Maternal mammary gland development was normal. There was no fetal NOAEL (no observable adverse effect level) established for this study because only one dose of 50 mg/kg was evaluated. Mammary gland histopathology at 6 months of age was normal in female offspring exposed to denosumab in utero; however, development and lactation have not been fully evaluated.

In RANKL knockout mice, absence of RANKL (the target of denosumab) also caused fetal lymph node agenesis and led to postnatal impairment of dentition and bone growth. Pregnant RANKL knockout mice showed altered maturation of the maternal mammary gland, leading to impaired lactation [see Use in Specific Populations (8.3) and Nonclinical Toxicology (13.2)].

8.2 Lactation

Risk Summary

There is no information regarding the presence of denosumab products in human milk, the effects on the breastfed child, or the effects on milk production. Denosumab was detected in the maternal milk of cynomolgus monkeys up to 1 month after the last dose of denosumab (≤ 0.5% milk:serum ratio) and maternal mammary gland development was normal, with no impaired lactation. However, pregnant RANKL knockout mice showed altered maturation of the maternal mammary gland, leading to impaired lactation [see Use in Specific Populations (8.1) and Nonclinical Toxicology (13.2)]. Consider the developmental and health benefits of breastfeeding along with the mother’s clinical need for Wyost treatment and any potential adverse effects on the breastfed child from Wyost or from the underlying maternal condition.

8.3 Females and Males of Reproductive Potential

Based on findings in animals and its mechanism of action, denosumab products can cause fetal harm when administered to a pregnant woman [see Use in Specific Populations (8.1)].

Pregnancy Testing

Verify the pregnancy status of females of reproductive potential prior to initiating Wyost treatment.

Contraception

Females

Advise females of reproductive potential to use effective contraception during therapy, and for at least 5 months after the last dose of Wyost.

8.4 Pediatric Use

The safety and efficacy of Wyost have not been established in pediatric patients except in skeletally mature adolescents (aged 12–16 years) with giant cell tumor of bone. Wyost is recommended only for treatment of skeletally mature adolescents (aged 12–16 years) with giant cell tumor of bone [see Indications and Usage (1.2)]. Clinically significant hypercalcemia after treatment discontinuation has been reported in pediatric patients with growing skeletons who received denosumab products for giant cell tumor of bone or for unapproved indications [see Adverse Reactions (6.2) and Warnings and Precautions (5.6)].

Denosumab was studied in an open-label trial that enrolled a subset of 19 adolescent patients (aged 12-16 years) with giant cell tumor of bone who had reached skeletal maturity, defined by at least 1 mature long bone (e.g., closed epiphyseal growth plate of the humerus), and had a body weight ≥ 45 kg [see Indications and Usage (1.2) and Clinical Trials (14.3)]. A total of one of five (20%) evaluable adolescent patients had an objective response by retrospective independent assessment of radiographic response according to modified Response Evaluation Criteria in Solid Tumors (RECIST 1.1). The adverse reaction profile and efficacy results appeared to be similar in skeletally mature adolescents and adults [see Adverse Reactions (6.1) and Clinical Trials (14.3)].

Animal Data

Treatment with denosumab products may impair bone growth in children with open growth plates and may inhibit eruption of dentition. In neonatal rats, inhibition of RANKL (the target of denosumab therapy) with a construct of osteoprotegerin bound to Fc (OPG-Fc) at doses ≤ 10 mg/kg was associated with inhibition of bone growth and tooth eruption. Adolescent primates treated with denosumab at doses 5 and 25 times (10 and 50 mg/kg dose) higher than the recommended human dose of 120 mg administered once every 4 weeks, based on body weight (mg/kg), had abnormal growth plates, considered to be consistent with the pharmacological activity of denosumab.

Cynomolgus monkeys exposed in utero to denosumab exhibited bone abnormalities, reduced hematopoiesis, tooth malalignment, decreased neonatal growth, and an absence of axillary, inguinal, mandibular, and mesenteric lymph nodes. Some bone abnormalities recovered once exposure was ceased following birth; however, axillary and inguinal lymph nodes remained absent 6 months post-birth [see Use in Specific Populations (8.1)].

8.5 Geriatric Use

Of the total number of patients in clinical studies that received denosumab (n = 2841) in Studies 20050136, 20050244, and 20050103, 1271 (44%) were ≥ 65 years old, while 473 patients (17%) were ≥ 75 years old. Of the 859 patients in Study 20090482 that received denosumab, 387 patients (45%) were ≥ 65 years old, while 141 patients (16%) were ≥ 75 years old. No overall differences in safety or efficacy were observed between older and younger patients.

8.6 Renal Impairment

Two clinical trials were conducted in patients without cancer and with varying degrees of renal function.

In one study, patients (N = 55) with varying degrees of renal function (ranging from normal through end-stage renal disease requiring dialysis) received a single 60 mg subcutaneous dose of denosumab. In a second study, patients (N = 32) with severe renal dysfunction (creatinine clearance less than 30 mL/min and/or on dialysis) were given two 120 mg subcutaneous doses of denosumab. In both studies, greater risk of developing hypocalcemia was observed with increasing renal impairment, and with inadequate/no calcium supplementation. Hypocalcemia was mild to moderate in severity in 96% of patients. Monitor calcium levels and calcium and vitamin D intake [see Warnings and Precautions (5.3), Adverse Reactions (6.1), and Clinical Pharmacology (12.3)].

10 OVERDOSAGE

There is no experience with overdosage of denosumab products.

11 DESCRIPTION

Denosumab-bbdz is a human IgG2 monoclonal antibody that binds to human RANKL. Denosumab-bbdz has an approximate molecular weight of 147 kDa and is produced in genetically engineered mammalian (Chinese hamster ovary) cells.

Wyost (denosumab-bbdz) injection is a sterile, preservative-free, clear to slightly opalescent and colorless to slightly yellowish to slightly brownish solution for subcutaneous use.

Each single-dose vial contains 1.7 mL solution of 120 mg denosumab-bbdz, glacial acetic acid (1.85 mg), polysorbate 20 (0.17 mg), sodium hydroxide (0.91 mg), sorbitol (78.9 mg), and Water for Injection (USP). Hydrochloric acid and sodium hydroxide may be added to adjust the pH to 5.2.

12 CLINICAL PHARMACOLOGY

12.1 Mechanism of Action

Denosumab products bind to RANKL, a transmembrane or soluble protein essential for the formation, function, and survival of osteoclasts, the cells responsible for bone resorption, thereby modulating calcium release from bone. Increased osteoclast activity, stimulated by RANKL, is a mediator of bone pathology in solid tumors with osseous metastases. Similarly, giant cell tumors of bone consist of stromal cells expressing RANKL and osteoclast-like giant cells expressing RANK receptor, and signaling through the RANK receptor contributes to osteolysis and tumor growth. Denosumab products prevent RANKL from activating its receptor, RANK, on the surface of osteoclasts, their precursors, and osteoclast-like giant cells.

12.2 Pharmacodynamics

In patients with breast cancer and bone metastases, the median reduction in uNTx/Cr was 82% within 1 week following initiation of denosumab 120 mg administered subcutaneously. In Studies 20050136, 20050244, and 20050103, the median reduction in uNTx/Cr from baseline to Month 3 was approximately 80% in 2075 denosumab-treated patients.

In a phase 3 study of patients with newly diagnosed multiple myeloma who received subcutaneous doses of denosumab 120 mg every 4 weeks (Q4W), median reductions in uNTx/Cr of approximately 75% were observed by Week 5. Reductions in bone turnover markers were maintained, with median reductions of 74% to 79% for uNTx/Cr from weeks 9 to 49 of continued 120 mg Q4W dosing.

In adult and skeletally mature adolescent patients with giant cell tumor of bone who received subcutaneous doses of denosumab 120 mg Q4W with a 120 mg loading dose on Days 8 and 15, median reductions in uNTx/Cr from baseline were 84% at Week 13 and 82% at Week 25.

12.3 Pharmacokinetics

Following subcutaneous administration, bioavailability was 62%. Denosumab displayed nonlinear pharmacokinetics at doses below 60 mg, but approximately dose-proportional increases in exposure at higher doses.

With multiple subcutaneous doses of 120 mg once every 4 weeks, up to 2.8-fold accumulation in serum denosumab concentrations was observed and steady-state was achieved by 6 months. A mean (± standard deviation) serum steady-state trough concentration of 20.5 (± 13.5) mcg/mL was achieved by 6 months. The mean elimination half-life was 28 days.

In patients with newly diagnosed multiple myeloma who received 120 mg every 4 weeks, denosumab concentrations appear to reach steady-state by Month 6. In patients with giant cell tumor of bone, after administration of subcutaneous doses of 120 mg once every 4 weeks with additional 120 mg doses on Days 8 and 15 of the first month of therapy, mean (± standard deviation) serum trough concentrations on Day 8, 15, and one month after the first dose were 19.0 (± 24.1), 31.6 (± 27.3), 36.4 (± 20.6) mcg/mL, respectively. Steady-state was achieved in 3 months after initiation of treatment with a mean serum trough concentration of 23.4 (± 12.1) mcg/mL.

Special Populations

Body Weight: A population pharmacokinetic analysis was performed to evaluate the effects of demographic characteristics. Denosumab clearance and volume of distribution were proportional to body weight. The steady-state exposure following repeat subcutaneous administration of 120 mg every 4 weeks to 45 kg and 120 kg subjects were, respectively, 48% higher and 46% lower than exposure of the typical 66 kg subject.

Age, Gender and Race: The pharmacokinetics of denosumab was not affected by age, gender, and race.

Pediatrics: In skeletally-mature adolescent patients (12 to 16 years of age) with giant cell tumor of bone (GCTB) who received 120 mg every 4 weeks with a 120 mg loading dose on Days 8 and 15, the pharmacokinetics of denosumab were comparable to those observed in adult patients with GCTB.

Hepatic Impairment: No clinical trials have been conducted to evaluate the effect of hepatic impairment on the pharmacokinetics of denosumab products.

Renal Impairment: In clinical trials of 87 patients with varying degrees of renal dysfunction, including patients on dialysis, the degree of renal impairment had no effect on the pharmacokinetics and pharmacodynamics of denosumab [see Use in Specific Populations (8.6)].

Drug Interactions

No formal drug-drug interaction trials have been conducted with denosumab. There was no evidence that various anticancer treatments affected denosumab systemic exposure and pharmacodynamic effect. Serum denosumab concentrations at 1 and 3 months and reductions in the bone turnover marker uNTx/Cr (urinary N-terminal telopeptide corrected for creatinine) at 3 months were similar in patients with and without prior intravenous bisphosphonate therapy and were not altered by concomitant chemotherapy and/or hormone therapy.

12.6 Immunogenicity

The observed incidence of anti-drug antibodies is highly dependent on the sensitivity and specificity of the assay. Differences in assay methods preclude meaningful comparisons of the incidence of anti-drug antibodies in the studies described below with the incidence of anti-drug antibodies in other studies, including those of denosumab or of other denosumab products.

Using an electrochemiluminescent bridging immunoassay, less than 1% (55 out of 8113) of patients treated with denosumab for up to 5 years tested positive for binding antibodies (including pre-existing, transient, and developing antibodies). None of the patients tested positive for neutralizing antibodies, as was assessed using a chemiluminescent cell-based in vitro biological assay. There was no identified clinically significant effect of anti-drug antibodies on pharmacokinetics, pharmacodynamics, safety, or effectiveness of denosumab.

13 NONCLINICAL TOXICOLOGY

13.1 Carcinogenesis, Mutagenesis, Impairment of Fertility

Carcinogenicity

The carcinogenic potential of denosumab products has not been evaluated in long-term animal studies.

Mutagenicity

The genotoxic potential of denosumab products has not been evaluated.

Impairment of Fertility

Denosumab had no effect on female fertility or male reproductive organs in monkeys at doses that were 6.5- to 25-fold higher than the recommended human dose of 120 mg subcutaneously administered once every 4 weeks, based on body weight (mg/kg).

13.2 Animal Toxicology and/or Pharmacology

Denosumab products are inhibitors of osteoclastic bone resorption via inhibition of RANKL.

Because the biological activity of denosumab in animals is specific to nonhuman primates, evaluation of genetically engineered (knockout) mice or use of other biological inhibitors of the RANK/RANKL pathway, OPG-Fc and RANK-Fc, provided additional information on the pharmacodynamic properties of denosumab. RANK/RANKL knockout mice exhibited absence of lymph node formation, as well as an absence of lactation due to inhibition of mammary gland maturation (lobulo-alveolar gland development during pregnancy). Neonatal RANK/RANKL knockout mice exhibited reduced bone growth and lack of tooth eruption. A corroborative study in 2-week-old rats given the RANKL inhibitor OPG-Fc also showed reduced bone growth, altered growth plates, and impaired tooth eruption. These changes were partially reversible in this model when dosing with the RANKL inhibitors was discontinued.

14 CLINICAL TRIALS

14.1 Bone Metastasis from Solid Tumors

The safety and efficacy of denosumab for the prevention of skeletal-related events in patients with bone metastases from solid tumors was demonstrated in three international, randomized (1:1), double-blind, active-controlled, noninferiority trials comparing denosumab with zoledronic acid. In all three trials, patients were randomized to receive 120 mg denosumab subcutaneously every 4 weeks or 4 mg zoledronic acid intravenously (IV) every 4 weeks (dose adjusted for reduced renal function). Patients with creatinine clearance less than 30 mL/min were excluded. In each trial, the main outcome measure was demonstration of noninferiority of time to first skeletal-related event (SRE) as compared to zoledronic acid. Supportive outcome measures were superiority of time to first SRE and superiority of time to first and subsequent SRE; testing for these outcome measures occurred if the main outcome measure was statistically significant. An SRE was defined as any of the following: pathologic fracture, radiation therapy to bone, surgery to bone, or spinal cord compression.

Study 20050136 (NCT00321464) enrolled 2046 patients with advanced breast cancer and bone metastasis. Randomization was stratified by a history of prior SRE (yes or no), receipt of chemotherapy within 6 weeks prior to randomization (yes or no), prior oral bisphosphonate use (yes or no), and region (Japan or other countries). Forty percent of patients had a previous SRE, 40% received chemotherapy within 6 weeks prior to randomization, 5% received prior oral bisphosphonates, and 7% were enrolled from Japan. Median age was 57 years, 80% of patients were White, and 99% of patients were women. The median number of doses administered was 18 for denosumab and 17 for zoledronic acid.

Study 20050244 (NCT00330759) enrolled 1776 adults with solid tumors other than breast and castrate-resistant prostate cancer with bone metastasis and multiple myeloma. Randomization was stratified by previous SRE (yes or no), systemic anticancer therapy at time of randomization (yes or no), and tumor type (non-small cell lung cancer, myeloma, or other). Eighty-seven percent were receiving systemic anticancer therapy at the time of randomization, 52% had a previous SRE, 64% of patients were men, 87% were White, and the median age was 60 years. A total of 40% of patients had non-small cell lung cancer, 10% had multiple myeloma, 9% had renal cell carcinoma, and 6% had small cell lung cancer. Other tumor types each comprised less than 5% of the enrolled population. The median number of doses administered was 7 for both denosumab and zoledronic acid.

Study 20050103 (NCT00321620) enrolled 1901 men with castrate-resistant prostate cancer and bone metastasis. Randomization was stratified by previous SRE, PSA level (less than 10 ng/mL or 10 ng/mL or greater) and receipt of chemotherapy within 6 weeks prior to randomization (yes or no). Twenty-six percent of patients had a previous SRE, 15% of patients had PSA less than 10 ng/mL, and 14% received chemotherapy within 6 weeks prior to randomization. Median age was 71 years and 86% of patients were White. The median number of doses administered was 13 for denosumab and 11 for zoledronic acid.

Denosumab delayed the time to first SRE following randomization as compared to zoledronic acid in patients with breast or castrate-resistant prostate cancer (CRPC) with osseous metastases (Table 2). In patients with bone metastasis due to other solid tumors or lytic lesions due to multiple myeloma, denosumab was noninferior to zoledronic acid in delaying the time to first SRE following randomization.

Overall survival and progression-free survival were similar between arms in all three trials.

Table 2. Efficacy Results for Denosumab Compared to Zoledronic Acid

 | Study 20050136; Metastatic Breast Cancer |  | Study 20050244; Metastatic Solid Tumors or Multiple Myeloma |  | Study 20050103; Metastatic CRPCa
 | Denosumab; N = 1026 | Zoledronic Acid; N = 1020 | Denosumab; N = 886 | Zoledronic Acid; N = 890 | Denosumab; N = 950 | Zoledronic Acid; N = 951
First On-study SRE
Number of Patients who had SREs (%) | 315 (30.7) | 372 (36.5) | 278 (31.4) | 323 (36.3) | 341 (35.9) | 386 (40.6)
Components of First SRE
Radiation to Bone | 82 (8.0) | 119 (11.7) | 119 (13.4) | 144 (16.2) | 177 (18.6) | 203 (21.3)
Pathological Fracture | 212 (20.7) | 238 (23.3) | 122 (13.8) | 139 (15.6) | 137 (14.4) | 143 (15.0)
Surgery to Bone | 12 (1.2) | 8 (0.8) | 13 (1.5) | 19 (2.1) | 1 (0.1) | 4 (0.4)
Spinal Cord Compression | 9 (0.9) | 7 (0.7) | 24 (2.7) | 21 (2.4) | 26 (2.7) | 36 (3.8)
Median Time to SRE (months) | NRb | 26.4 | 20.5 | 16.3 | 20.7 | 17.1
Hazard Ratio (95% CI) | 0.82 (0.71, 0.95) |  | 0.84 (0.71, 0.98) |  | 0.82 (0.71, 0.95)
Noninferiority p-value | < 0.001 |  | < 0.001 |  | < 0.001
Superiority p-valuec | 0.010 |  | 0.060 |  | 0.008
First and Subsequent SREd
Mean Number/Patient | 0.46 | 0.60 | 0.44 | 0.49 | 0.52 | 0.61
Rate Ratio (95% CI) | 0.77 (0.66, 0.89) |  | 0.90 (0.77, 1.04) |  | 0.82 (0.71, 0.94)
Superiority p-valuee | 0.001 |  | 0.145 |  | 0.009

a CRPC = castrate-resistant prostate cancer.

b NR = not reached.

c Superiority testing performed only after denosumab demonstrated to be noninferior to zoledronic acid within trial.

d All skeletal events postrandomization; new events defined by occurrence ≥ 21 days after preceding event.

e Adjusted p-values are presented.

14.2 Multiple Myeloma

The efficacy of denosumab for the prevention of skeletal-related events in newly diagnosed multiple myeloma patients with treatment through disease progression, was evaluated in Study 20090482 (NCT01345019), an international, randomized (1:1), double-blind, active-controlled, noninferiority trial comparing denosumab with zoledronic acid. In this trial, patients were randomized to receive 120 mg denosumab subcutaneously every 4 weeks or 4 mg zoledronic acid intravenously (IV) every 4 weeks (dose adjusted for reduced renal function). Patients with creatinine clearance less than 30 mL/min were excluded. In this trial, the main efficacy outcome measure was noninferiority of time to first skeletal-related event (SRE). Additional efficacy outcome measures were superiority of time to first SRE, time to first and subsequent SRE, and overall survival. An SRE was defined as any of the following: pathologic fracture, radiation therapy to bone, surgery to bone, or spinal cord compression.

Study 20090482 enrolled 1718 newly diagnosed multiple myeloma patients with bone lesions. Randomization was stratified by a history of prior SRE (yes or no), the anti-myeloma agent being utilized/planned to be utilized in first-line therapy (novel therapy-based or non-novel therapy-based [novel therapies include bortezomib, lenalidomide, or thalidomide]), intent to undergo autologous PBSC transplantation (yes or no), stage at diagnosis (International Staging System I or II or III) and region Japan (yes or no). At study enrollment, 96% of the patients were receiving or planning to receive novel therapy-based first-line anti-myeloma therapy, 55% of the patients intended to undergo autologous PBSC transplantation, 61% of patients had a previous SRE, 32% were at ISS Stage I, 38% were at ISS Stage II and 29% were at ISS Stage III, and 2% were enrolled from Japan. Median age was 63 years, 82% of patients were White, and 46% of patients were women. The median number of doses administered was 16 for denosumab and 15 for zoledronic acid.

Denosumab was noninferior to zoledronic acid in delaying the time to first SRE following randomization (HR = 0.98, 95% CI, 0.85-1.14). The results for overall survival (OS) were comparable between denosumab and zoledronic acid treatment groups with a hazard ratio of 0.90 (95% CI: 0.70, 1.16).

Table 3. Efficacy Results for Denosumab Compared to Zoledronic Acid

 | Study 20090482; Multiple Myeloma
 | Denosumab; N = 859 | Zoledronic Acid; N = 859
First On-study SRE
Number of Patients who had SREs (%) | 376 (43.8) | 383 (44.6)
Components of First SRE
Radiation to Bone | 47 (5.5) | 62 (7.2)
Pathological Fracture | 342 (39.8) | 338 (39.3)
Surgery to Bone | 37 (4.3) | 48 (5.6)
Spinal Cord Compression | 6 (0.7) | 4 (0.5)
Median Time to SRE (months); (95% CI) | 22.8; (14.7, NEa) | 24; (16.6, 33.3)
Hazard Ratio (95% CI) | 0.98 (0.85, 1.14)

a NE = not estimable

14.3 Giant Cell Tumor of Bone

The safety and efficacy of denosumab for the treatment of giant cell tumor of bone in adults or skeletally mature adolescents were demonstrated in two open-label trials [Study 20040215 (NCT00396279) and Study 20062004 (NCT00680992)] that enrolled patients with histologically confirmed measurable giant cell tumor of bone that was either recurrent, unresectable, or for which planned surgery was likely to result in severe morbidity. Patients received 120 mg denosumab subcutaneously every 4 weeks with a loading dose on Days 8 and 15 of the first cycle of therapy. Patients who discontinued denosumab then entered the safety follow-up phase for a minimum of 60 months. Retreatment with denosumab while in safety follow-up was allowed for patients who initially demonstrated a response to denosumab (e.g., in the case of recurrent disease).

Study 20040215 was a single-arm, pharmacodynamic, and proof of concept trial conducted in 37 adult patients with unresectable or recurrent giant cell tumor of bone. Patients were required to have histologically confirmed giant cell tumor of bone and radiologic evidence of measurable disease from a computed tomography (CT) or magnetic resonance imaging (MRI) obtained within 28 days prior to study enrollment. Patients enrolled in Study 20040215 underwent CT or MRI assessment of giant cell tumor of bone at baseline and quarterly during denosumab treatment.

Study 20062004 was a parallel-cohort, proof of concept, and safety trial conducted in 535 adult or skeletally mature adolescent patients with histologically confirmed giant cell tumor of bone and evidence of measurable active disease. Study 20062004 enrolled 19 patients who were 12-16 years of age [see Use in Specific Populations (8.4)]. Patients enrolled into one of three cohorts: Cohort 1 enrolled 268 patients with surgically unsalvageable disease (e.g., sacral or spinal sites of disease, or pulmonary metastases); Cohort 2 enrolled 252 patients with surgically salvageable disease where the investigator determined that the planned surgery was likely to result in severe morbidity (e.g., joint resection, limb amputation, or hemipelvectomy); Cohort 3 enrolled 15 patients who previously participated in Study 20040215. Patients underwent imaging assessment of disease status at intervals determined by their treating physician.

A retrospective interim analysis concluded by an independent review committee evaluated objective response in 187 patients enrolled and treated in Study 20040215 and Study 20062004 for whom baseline and at least one post-baseline radiographic assessment were available (27 of 37 patients enrolled in Study 20040215 and 160 of 270 patients enrolled in Cohorts 1 and 2 of Study 20062004). The primary efficacy outcome measure was objective response rate using Response Evaluation Criteria in Solid Tumors (RECIST) v 1.1.

The overall objective response rate (RECIST 1.1) was 25% (95% CI: 19, 32). All responses were partial responses. The estimated median time to response was 3 months. In the 47 patients with an objective response, the median duration of follow-up was 20 months (range: 2-44 months), and 51% (24/47) had a duration of response lasting at least 8 months. Three patients experienced disease progression following an objective response.

14.4 Hypercalcemia of Malignancy

The safety and efficacy of denosumab was demonstrated in an open-label, single-arm trial [Study 20070315 (NCT00896454)] that enrolled 33 patients with hypercalcemia of malignancy (with or without bone metastases) refractory to treatment with intravenous bisphosphonate therapy. Patients received denosumab subcutaneously every 4 weeks with additional 120 mg doses on Days 8 and 15 of the first month of therapy.

In this trial, refractory hypercalcemia of malignancy was defined as an albumin-corrected calcium of > 12.5 mg/dL (3.1 mmol/L) despite treatment with intravenous bisphosphonate therapy in 7-30 days prior to initiation of denosumab therapy. The primary outcome measure was the proportion of patients achieving a response, defined as corrected serum calcium (CSC) ≤ 11.5 mg/dL (2.9 mmol/L), within 10 days after denosumab administration. Efficacy data are summarized in Figure 1 and Table 4. Concurrent chemotherapy did not appear to affect response to denosumab.

Figure 1. Corrected Serum Calcium by Visit in Responders (Median and Interquartile Range)

N = Number of responders who received ≥ 1 dose of investigational product
n = Number of responders who had no missing data at baseline and the time point of interest

Table 4. Efficacy in Patients with Hypercalcemia of Malignancy Refractory to Bisphosphonate Therapy

 | N = 33 | Proportion (%); (95% CI)
All Responders (CSC ≤ 11.5 mg/dL) by Day 10 | 21 | 63.6; (45.1, 79.6)
All Responders by Day 57 | 23 | 69.7; (51.3, 84.4)
Complete Responders (CSC ≤ 10.8 mg/dL) by Day 10 | 12 | 36.4; (20.4, 54.9)
All Complete Responders by Day 57 | 21 | 63.6; (45.1, 79.6)

Median time to response (CSC ≤ 11.5 mg/dL) was 9 days (95% CI: 8, 19), and the median duration of response was 104 days (95% CI: 7, not estimable). Median time to complete response (CSC ≤ 10.8 mg/dL) was 23 days (95% CI: 9, 36), and the median duration of complete response was 34 days (95% CI: 1, 134).

16 HOW SUPPLIED/STORAGE AND HANDLING

Wyost injection is a clear to slightly opalescent and colorless to slightly yellowish to slightly brownish solution supplied in a single-dose vial. The vial stopper is not made with natural rubber latex.

120 mg/1.7 mL (70 mg/mL) | 1 vial per carton | NDC 61314-228-94

Store Wyost refrigerated at 2°C to 8°C (36°F to 46°F) in the original carton to protect from light. Do not freeze. Prior to administration, Wyost may be allowed to reach room temperature up to 25°C (77°F) in the original container. Once removed from the refrigerator, Wyost must not be exposed to temperatures above 25°C (77°F) and must be used within 30 days. Discard Wyost if not used within the 30 days. Do not use Wyost after the expiry date printed on the label.

Protect Wyost from direct light and heat.

Avoid vigorous shaking of Wyost.

17 PATIENT COUNSELING INFORMATION

Drug Products with Same Active Ingredient

Advise patients that if they receive Wyost, they should not receive other denosumab products concomitantly [see Warnings and Precautions (5.1)].

Hypersensitivity

Advise patients to seek prompt medical attention if signs or symptoms of hypersensitivity reactions occur. Advise patients who have had signs or symptoms of systemic hypersensitivity reactions that they should not receive denosumab products [see Warnings and Precautions (5.2) and Contraindications (4.2)].

Hypocalcemia

Adequately supplement patients with calcium and vitamin D and instruct them on the importance of maintaining serum calcium levels while receiving Wyost [see Warnings and Precautions (5.3) and Use in Specific Populations (8.6)]. Advise patients to seek prompt medical attention if they develop signs or symptoms of hypocalcemia.

Osteonecrosis of the Jaw

Advise patients to maintain good oral hygiene during treatment with Wyost and to inform their dentist prior to dental procedures that they are receiving Wyost. Patients should avoid invasive dental procedures during treatment with Wyost and inform their healthcare provider or dentist if they experience persistent pain and/or slow healing of the mouth or jaw after dental surgery [see Warnings and Precautions (5.4)].

Atypical Subtrochanteric and Diaphyseal Femoral Fracture

Advise patients to report new or unusual thigh, hip, or groin pain [see Warnings and Precautions (5.5)].

Hypercalcemia Following Treatment Discontinuation in Patients with Giant Cell Tumor of Bone and in Patients with Growing Skeletons

Advise patients to report nausea, vomiting, headache, and decreased alertness following treatment discontinuation [see Warnings and Precautions (5.6) and Use in Specific Populations (8.4)].

Multiple Vertebral Fractures (MVF) Following Treatment Discontinuation

Advise patients that after treatment with Wyost is stopped there may be an increased risk of having broken bones in the spine especially in patients who have had a fracture or who have had osteoporosis. Advise patients not to interrupt Wyost therapy without their physician’s advice [see Warnings and Precautions (5.7)].

Embryo-Fetal Toxicity

Advise females of reproductive potential that Wyost can cause harm to a fetus and to inform their healthcare provider of a known or suspected pregnancy [see Warnings and Precautions (5.8) and Use in Specific Populations (8.1, 8.3)].

Advise females of reproductive potential to use effective contraception during treatment and for at least 5 months after the last dose of Wyost [see Use in Specific Populations (8.3)].

Wyost® (denosumab-bbdz)

Manufactured by:
Sandoz Inc.
Princeton, NJ 08540
U.S. License No. 2003

XGEVA® is a registered trademark of Amgen Inc.

PRINCIPAL DISPLAY PANEL

NDC 61314-228-94

Rx only

Wyost®

(denosumab-bbdz)

Injection

120 mg/1.7 mL

(70 mg/mL)

For Subcutaneous Use Only

For more information please visit www.wyost.com or call 1-800-525-8747.

1 x 120 mg Single-Dose Vial

Discard Unused Portion.

Sterile Solution – No Preservative

Wyost should be administered by a healthcare provider.

SANDOZ